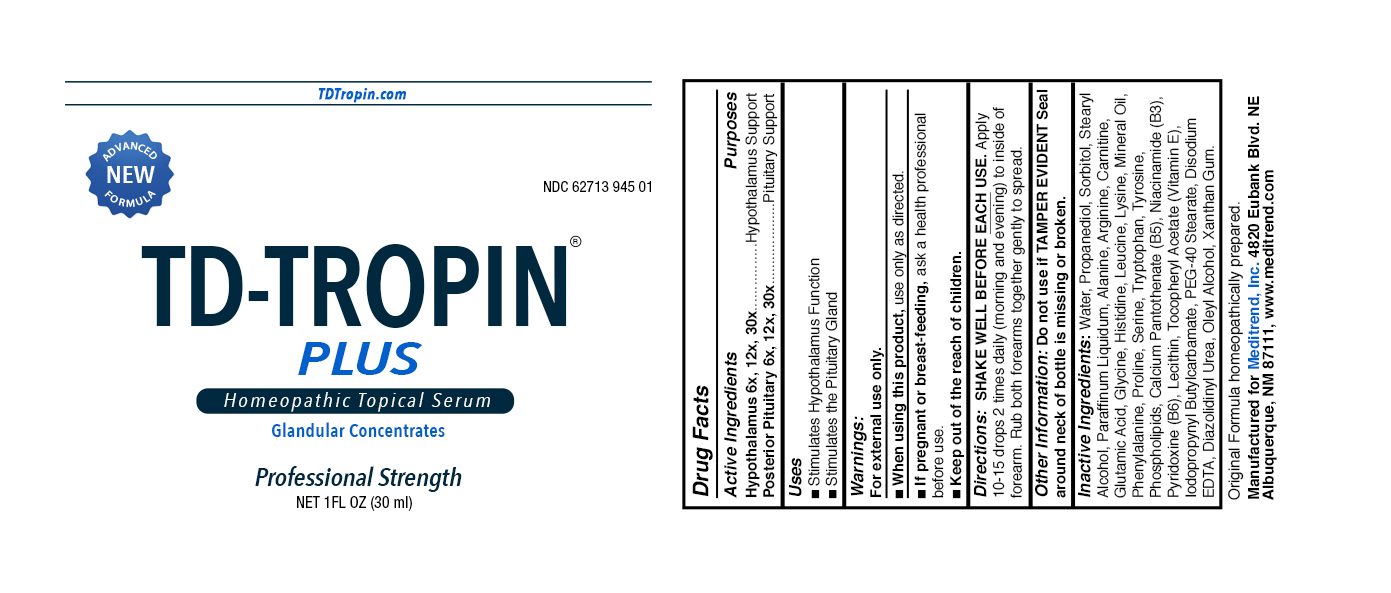 DRUG LABEL: Meditrend
NDC: 62713-945 | Form: LIQUID
Manufacturer: Meditrend, Inc. DBA Progena Professional Formulations
Category: homeopathic | Type: HUMAN OTC DRUG LABEL
Date: 20151201

ACTIVE INGREDIENTS: BOS TAURUS HYPOTHALAMUS 30 [hp_X]/1 mL; BOS TAURUS PITUITARY GLAND 30 [hp_X]/1 mL
INACTIVE INGREDIENTS: WATER; PROPANEDIOL; SORBITOL; STEARYL ALCOHOL; PARAFFIN; ALANINE; ARGININE; CARNITINE; GLUTAMIC ACID; GLYCINE; HISTIDINE; LEUCINE; LYSINE; PHENYLALANINE; PROLINE; SERINE; TRYPTOPHAN; TYROSINE; EGG PHOSPHOLIPIDS; CALCIUM PANTOTHENATE; NIACINAMIDE; PYRIDOXINE; LECITHIN, SOYBEAN; .ALPHA.-TOCOPHEROL ACETATE; IODOPROPYNYL BUTYLCARBAMATE; PEG-40 STEARATE; EDETATE DISODIUM; DIAZOLIDINYL UREA; OLEYL ALCOHOL; XANTHAN GUM

TD-TROPIN PLUS

ACTIVE INGREDIENT

Active Ingredients: Hypothalamus 6x, 12x, 30x. Pituitary 6x, 12x, 30x.

PURPOSE

Purpose: To Improve the Quality of Health and Well-being.

INDICATIONS AND USAGE

Use:Homeopathic Serum to Restore and Maintain Balanced
Hormonal Regulation and Vital Body Functions.

Warnings:
For external use only.

- Use Only as directed.
- If pregnant or breast-feeding, do not use this product.

Keep Out of Reach of Children. In case of overdose,
seek medical assistance or contact a Poison Control Center
immediately.

DOSAGE AND ADMINISTRATION

Directions: SHAKE WELL BEFORE EACH USE. Apply
10-15 drops 2 times daily (morning and evening) to inside of
forearm. Rub both forearms together gently to spread.

Other Information: Do not use if TAMPER EVIDENT seal
around neck of bottle is missing or broken.

Inactive Ingredients: Water, Propanediol, Sorbitol, Stearyl
Alcohol, Paraffinum Liquidum, Alanine, Arginine, Carnitine,
Glutamic Acid, Clycine, Histidine, Leucine, Lysine,
Phenylalanine, Proline, Serine, Tryptophan, Tyrosine,
Phospholipids, Calcium Pantothenate (B5), Niacinamide (B3),
Pyridoxine (B6), Lecithin, Tocopheryl Acetate (Vitamin E),
Iodopropynyl Butylcarbamate, PEG-40 Stearate, Disodium
EDTA, Diazolidinyl Urea, Oleyl Alcohol, Xanthan Gum.

PACKAGE LABEL

Original Formula homeopathically prepared.

Manufactured for Meditrend, Inc. 4820 Eubank Blvd. NE
Albuquerque, NM 87111, www.meditrend.com